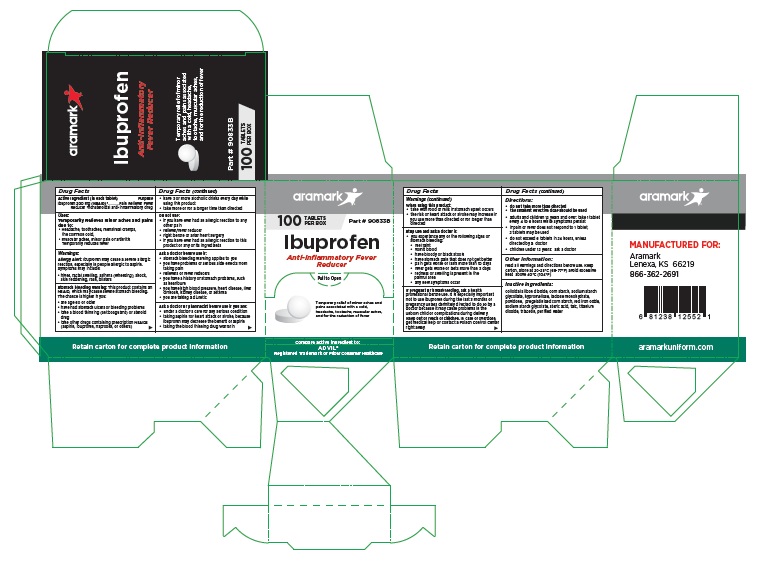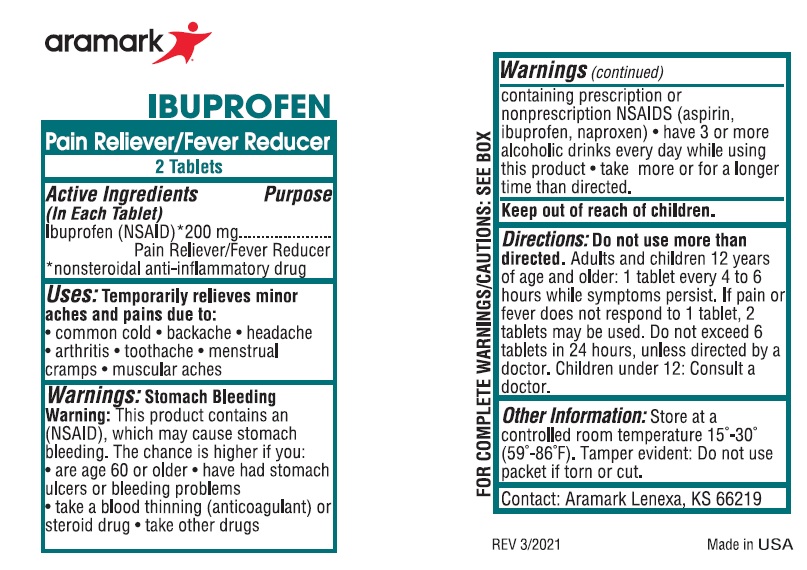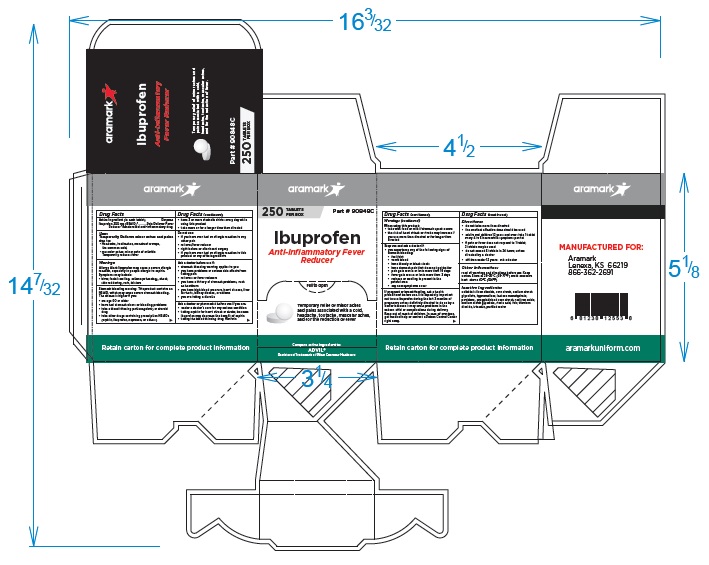 DRUG LABEL: Aramark Ibuprofen
NDC: 81238-0103 | Form: TABLET
Manufacturer: Western First Aid Safety DBA Aramark
Category: otc | Type: HUMAN OTC DRUG LABEL
Date: 20210520

ACTIVE INGREDIENTS: IBUPROFEN 200 mg/1 1
INACTIVE INGREDIENTS: SILICON DIOXIDE; STARCH, CORN; SODIUM STARCH GLYCOLATE TYPE A; HYPROMELLOSE, UNSPECIFIED; LACTOSE MONOHYDRATE; POVIDONE; FERRIC OXIDE RED; STEARIC ACID; TALC; TITANIUM DIOXIDE; TRIACETIN; WATER

Aramark Ibuprofen

Drug Facts

Active Ingredient (in each tablet)
Ibuprofen 200 mg (NSAID)*

Purpose
Ibuprofen 200 mg (NSAID)*.............Pain Reliever Fever Reducer

*nonsteroidal anti-inflammatory drug

Uses:
Temporarily Relieves minor aches and pains
due to:
• Headache, toothaches, menstrual cramps,
the common cold,
• muscular aches, minor pain of arthritis
Temporarily reduces fever

Warnings:

Allergy Alert: Ibuprofen may cause a severe allergic
reaction, especially in people allergic to aspirin.
Symptoms may include:
• hives, facial swelling, asthma (wheezing), shock,
skin reddening, rash, blisters

Stomach bleeding warning: This product contains an
NSAID, which may cause severe stomach bleeding.
The chance is higher if you:
• are age 60 or older
• have had stomach ulcers or bleeding problems
• take a blood thinning (anticoagulant) or steroid
drug
• take other drugs containing prescription NSAIDs
(aspirin, ibuprofen, naproxen, or others)
• have 3 or more alcoholic drinks every day while
using this product
• take more or for a longer time than directed

Do not use:
• if you have ever had an allergic reaction to any
other pain
• reliever/fever reducer
• right before or after heart surgery
• if you have ever had an allergic reaction to this
product or any of its ingredients

Ask a doctor before use if:
• stomach bleeding warning applies to you
• you have problems or serious side effects from
taking pain
• relievers or fever reducers
• you have a history of stomach problems, such
as heartburn
• you have high blood pressure, heart disease, liver
cirrhosis, kidney disease, or asthma
• you are taking a diuretic

Ask a doctor or pharmacist before use if you are:
• under a doctor’s care for any serious condition
• taking aspirin for heart attack or stroke, because
ibuprofen may decrease the benefit of aspirin
• taking the blood thinning drug Warfarin

When using this product:
• take with food or milk if stomach upset occurs
• the risk of heart attack or stroke may increase if
you use more than directed or for longer than
directed

Stop use and ask a doctor if:
• you experience any of the following signs of
stomach bleeding:
• feel faint
• vomit blood
• have bloody or black stools
• have stomach pain that does not get better
• pain gets worse or lasts more than 10 days
• fever gets worse or lasts more than 3 days
• redness or swelling is present in the
painful area
• any new symptoms occur

If pregnant or breast-feeding, ask a health
professional before use. It is especially important
not to use ibuprofen during the last 3 months of
pregnancy unless definitely directed to do so by a
doctor because it may cause problems in the
unborn child or complications during delivery.

Keep out of reach of children. In case of overdose,
get medical help or contact a Poison Control Center
right away.

Directions:
• do not take more than directed
• the smallest effective dose should be used
• adults and children 12 years and over: take 1 tablet
every 4 to 6 hours while symptoms persist
• if pain or fever does not respond to 1 tablet,
2 tablets may be used
• do not exceed 6 tablets in 24 hours, unless
directed by a doctor
• children under 12 years: ask a doctor

Other information:
read all warnings and directions before use. Keep
carton. Store at 20-25°C (68-77°F) avoid excessive
heat above 40°C (104°F)

Inactive Ingredients:
colloidal silicon dioxide, corn starch, sodium starch
glycollate, hypromellose, lactose monohydrate,
povidone, pregelatinized corn starch, red iron oxide,
sodium starch glycolate, steric acid, talc, titanium
dioxide, triacetin, purified water

Product Package

aramark

100 TABLETS PER BOX Part # 552R23

Ibuprofen
Anti-Inflammatory Fever
Reducer

Compare active ingredient to:

ADVIL®
Registered Trademark of Pfizer Consumer Healthcare

Retain carton for complete product information

MANUFACTURED FOR:
Aramark
Lenexa, KS 66219
(913) 269-9611

aramarkuniform.com

100 Tablet Box

250 Tablet Box

2-Tablet Packet

res